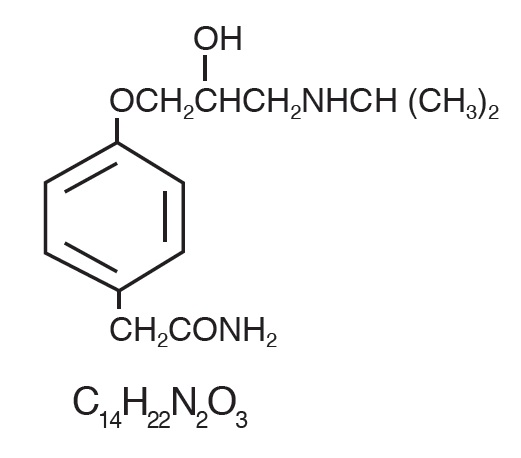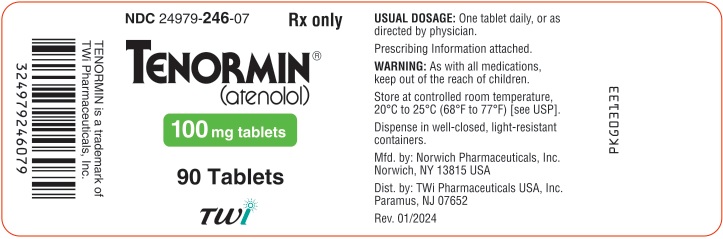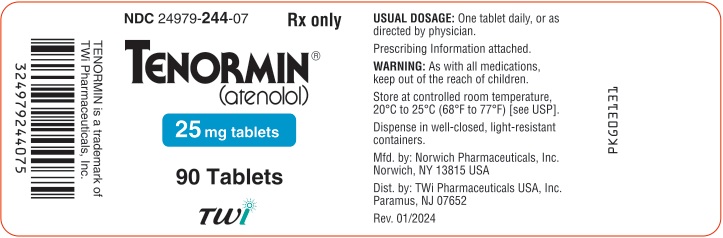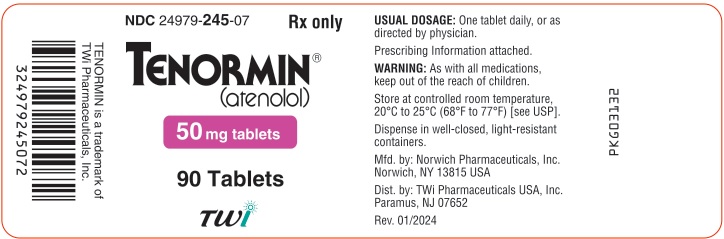 DRUG LABEL: TENORMIN
NDC: 24979-244 | Form: TABLET
Manufacturer: Upsher-Smith Laboratories, LLC
Category: prescription | Type: HUMAN PRESCRIPTION DRUG LABEL
Date: 20240805

ACTIVE INGREDIENTS: ATENOLOL 25 mg/1 1
INACTIVE INGREDIENTS: MAGNESIUM STEARATE; MICROCRYSTALLINE CELLULOSE; SODIUM STARCH GLYCOLATE TYPE A POTATO; POVIDONE, UNSPECIFIED

TENORMIN®
(atenolol) Tablets

DESCRIPTION

TENORMIN® (atenolol), a synthetic, beta1-selective (cardioselective) adrenoreceptor blocking agent, may be chemically described as benzeneacetamide, 4 -[2'-hydroxy-3'-[(1- methylethyl) amino] propoxy]-. The molecular and structural formulas are:

Atenolol (free base) has a molecular weight of 266. It is a relatively polar hydrophilic compound with a water solubility of 26.5 mg/mL at 37°C and a log partition coefficient (octanol/water) of 0.23. It is freely soluble in 1N HCl (300 mg/mL at 25°C) and less soluble in chloroform (3 mg/mL at 25°C).

TENORMIN is available as 25 mg, 50 mg and 100 mg tablets for oral administration.

Inactive Ingredients: Magnesium stearate, microcrystalline cellulose, povidone, sodium starch glycolate.

CLINICAL PHARMACOLOGY

TENORMIN is a beta1-selective (cardioselective) beta-adrenergic receptor blocking agent without membrane stabilizing or intrinsic sympathomimetic (partial agonist) activities. This preferential effect is not absolute, however, and at higher doses, TENORMIN inhibits beta2-adrenoreceptors, chiefly located in the bronchial and vascular musculature.

Pharmacokinetics and Metabolism

In man, absorption of an oral dose is rapid and consistent but incomplete. Approximately 50% of an oral dose is absorbed from the gastrointestinal tract, the remainder being excreted unchanged in the feces. Peak blood levels are reached between two (2) and four (4) hours after ingestion. Unlike propranolol or metoprolol, but like nadolol, TENORMIN undergoes little or no metabolism by the liver, and the absorbed portion is eliminated primarily by renal excretion. Over 85% of an intravenous dose is excreted in urine within 24 hours compared with approximately 50% for an oral dose. TENORMIN also differs from propranolol in that only a small amount (6% to 16%) is bound to proteins in the plasma. This kinetic profile results in relatively consistent plasma drug levels with about a 4-fold interpatient variation.

The elimination half-life of oral TENORMIN is approximately 6 to 7 hours, and there is no alteration of the kinetic profile of the drug by chronic administration. Following intravenous administration, peak plasma levels are reached within 5 minutes. Declines from peak levels are rapid (5- to 10-fold) during the first 7 hours; thereafter, plasma levels decay with a half-life similar to that of orally administered drug. Following oral doses of 50 mg or 100 mg, both beta-blocking and antihypertensive effects persist for at least 24 hours. When renal function is impaired, elimination of TENORMIN is closely related to the glomerular filtration rate; significant accumulation occurs when the creatinine clearance falls below 35 mL/min/1.73m^2. (See DOSAGE AND ADMINISTRATION.)

Pharmacodynamics

In standard animal or human pharmacological tests, beta-adrenoreceptor blocking activity of TENORMIN has been demonstrated by: (1) reduction in resting and exercise heart rate and cardiac output, (2) reduction of systolic and diastolic blood pressure at rest and on exercise, (3) inhibition of isoproterenol induced tachycardia, and (4) reduction in reflex orthostatic tachycardia.

A significant beta-blocking effect of TENORMIN, as measured by reduction of exercise tachycardia, is apparent within one hour following oral administration of a single dose. This effect is maximal at about 2 to 4 hours, and persists for at least 24 hours. Maximum reduction in exercise tachycardia occurs within 5 minutes of an intravenous dose. For both orally and intravenously administered drug, the duration of action is dose related and also bears a linear relationship to the logarithm of plasma TENORMIN concentration. The effect on exercise tachycardia of a single 10 mg intravenous dose is largely dissipated by 12 hours, whereas beta-blocking activity of single oral doses of 50 mg and 100 mg is still evident beyond 24 hours following administration. However, as has been shown for all beta-blocking agents, the antihypertensive effect does not appear to be related to plasma level.

In normal subjects, the beta1 selectivity of TENORMIN has been shown by its reduced ability to reverse the beta2-mediated vasodilating effect of isoproterenol as compared to equivalent beta-blocking doses of propranolol. In asthmatic patients, a dose of TENORMIN producing a greater effect on resting heart rate than propranolol resulted in much less increase in airway resistance. In a placebo controlled comparison of approximately equipotent oral doses of several beta-blockers, TENORMIN produced a significantly smaller decrease of FEV1 than nonselective beta-blockers such as propranolol and, unlike those agents, did not inhibit bronchodilation in response to isoproterenol.

Consistent with its negative chronotropic effect due to beta blockade of the SA node, TENORMIN increases sinus cycle length and sinus node recovery time. Conduction in the AV node is also prolonged. TENORMIN is devoid of membrane stabilizing activity, and increasing the dose well beyond that producing beta blockade does not further depress myocardial contractility. Several studies have demonstrated a moderate (approximately 10%) increase in stroke volume at rest and during exercise.

In controlled clinical trials, TENORMIN, given as a single daily oral dose, was an effective antihypertensive agent providing 24-hour reduction of blood pressure. TENORMIN has been studied in combination with thiazide type diuretics, and the blood pressure effects of the combination are approximately additive. TENORMIN is also compatible with methyldopa, hydralazine, and prazosin, each combination resulting in a larger fall in blood pressure than with the single agents. The dose range of TENORMIN is narrow and increasing the dose beyond 100 mg once daily is not associated with increased antihypertensive effect. The mechanisms of the antihypertensive effects of beta-blocking agents have not been established. Several possible mechanisms have been proposed and include: (1) competitive antagonism of catecholamines at peripheral (especially cardiac) adrenergic neuron sites, leading to decreased cardiac output, (2) a central effect leading to reduced sympathetic outflow to the periphery, and (3) suppression of renin activity. The results from long-term studies have not shown any diminution of the antihypertensive efficacy of TENORMIN with prolonged use.

By blocking the positive chronotropic and inotropic effects of catecholamines and by decreasing blood pressure, atenolol generally reduces the oxygen requirements of the heart at any given level of effort, making it useful for many patients in the long-term management of angina pectoris. On the other hand, atenolol can increase oxygen requirements by increasing left ventricular fiber length and end diastolic pressure, particularly in patients with heart failure.

In a multicenter clinical trial (ISIS-1) conducted in 16,027 patients with suspected myocardial infarction, patients presenting within 12 hours (mean = 5 hours) after the onset of pain were randomized to either conventional therapy plus TENORMIN (n = 8,037), or conventional therapy alone (n = 7,990). Patients with a heart rate of < 50 bpm or systolic blood pressure < 100 mm Hg, or with other contraindications to beta blockade were excluded. Thirty-eight percent of each group were treated within 4 hours of onset of pain. The mean time from onset of pain to entry was 5.0 ± 2.7 hours in both groups. Patients in the TENORMIN group were to receive TENORMIN I.V. Injection 5 mg to 10 mg given over 5 minutes plus TENORMIN Tablets 50 mg every 12 hours orally on the first study day (the first oral dose administered about 15 minutes after the I.V. dose) followed by either TENORMIN Tablets 100 mg once daily or TENORMIN Tablets 50 mg twice daily on days 2 to 7. The groups were similar in demographic and medical history characteristics and in electrocardiographic evidence of myocardial infarction, bundle branch block, and first degree atrioventricular block at entry.

During the treatment period (days 0 to 7), the vascular mortality rates were 3.89% in the TENORMIN group (313 deaths) and 4.57% in the control group (365 deaths). This absolute difference in rates, 0.68%, is statistically significant at the P < 0.05 level. The absolute difference translates into a proportional reduction of 15% (3.89-4.57/4.57 = -0.15). The 95% confidence limits are 1% to 27%. Most of the difference was attributed to mortality in days 0 to 1 (TENORMIN - 121 deaths; control - 171 deaths).

Despite the large size of the ISIS-1 trial, it is not possible to identify clearly subgroups of patients most likely or least likely to benefit from early treatment with atenolol. Good clinical judgment suggests, however, that patients who are dependent on sympathetic stimulation for maintenance of adequate cardiac output and blood pressure are not good candidates for beta blockade. Indeed, the trial protocol reflected that judgment by excluding patients with blood pressure consistently below 100 mm Hg systolic. The overall results of the study are compatible with the possibility that patients with borderline blood pressure (less than 120 mm Hg systolic), especially if over 60 years of age, are less likely to benefit.

The mechanism through which atenolol improves survival in patients with definite or suspected acute myocardial infarction is unknown, as is the case for other beta-blockers in the postinfarction setting. Atenolol, in addition to its effects on survival, has shown other clinical benefits including reduced frequency of ventricular premature beats, reduced chest pain, and reduced enzyme elevation.

Atenolol Geriatric Pharmacology:

In general, elderly patients present higher atenolol plasma levels with total clearance values about 50% lower than younger subjects. The half-life is markedly longer in the elderly compared to younger subjects. The reduction in atenolol clearance follows the general trend that the elimination of renally excreted drugs is decreased with increasing age.

INDICATIONS AND USAGE

Hypertension

TENORMIN is indicated for the treatment of hypertension, to lower blood pressure. Lowering blood pressure lowers the risk of fatal and non-fatal cardiovascular events, primarily strokes and myocardial infarctions. These benefits have been seen in controlled trials of antihypertensive drugs from a wide variety of pharmacologic classes including atenolol.

Control of high blood pressure should be part of comprehensive cardiovascular risk management, including, as appropriate, lipid control, diabetes management, antithrombotic therapy, smoking cessation, exercise, and limited sodium intake. Many patients will require more than 1 drug to achieve blood pressure goals. For specific advice on goals and management, see published guidelines, such as those of the National High Blood Pressure Education Program’s Joint National Committee on Prevention, Detection, Evaluation, and Treatment of High Blood Pressure (JNC).

Numerous antihypertensive drugs, from a variety of pharmacologic classes and with different mechanisms of action, have been shown in randomized controlled trials to reduce cardiovascular morbidity and mortality, and it can be concluded that it is blood pressure reduction, and not some other pharmacologic property of the drugs, that is largely responsible for those benefits. The largest and most consistent cardiovascular outcome benefit has been a reduction in the risk of stroke, but reductions in myocardial infarction and cardiovascular mortality also have been seen regularly.

Elevated systolic or diastolic pressure causes increased cardiovascular risk, and the absolute risk increase per mmHg is greater at higher blood pressures, so that even modest reductions of severe hypertension can provide substantial benefit. Relative risk reduction from blood pressure reduction is similar across populations with varying absolute risk, so the absolute benefit is greater in patients who are at higher risk independent of their hypertension (for example, patients with diabetes or hyperlipidemia), and such patients would be expected to benefit from more aggressive treatment to a lower blood pressure goal.

Some antihypertensive drugs have smaller blood pressure effects (as monotherapy) in black patients, and many antihypertensive drugs have additional approved indications and effects (e.g., on angina, heart failure, or diabetic kidney disease). These considerations may guide selection of therapy.

TENORMIN may be administered with other antihypertensive agents.

Angina Pectoris Due to Coronary Atherosclerosis

TENORMIN is indicated for the long-term management of patients with angina pectoris.

Acute Myocardial Infarction

TENORMIN is indicated in the management of hemodynamically stable patients with definite or suspected acute myocardial infarction to reduce cardiovascular mortality. Treatment can be initiated as soon as the patient’s clinical condition allows. (See DOSAGE AND ADMINISTRATION, CONTRAINDICATIONS, and WARNINGS.) In general, there is no basis for treating patients like those who were excluded from the ISIS-1 trial (blood pressure less than 100 mm Hg systolic, heart rate less than 50 bpm) or have other reasons to avoid beta blockade. As noted above, some subgroups (e.g., elderly patients with systolic blood pressure below 120 mm Hg) seemed less likely to benefit.

CONTRAINDICATIONS

TENORMIN is contraindicated in sinus bradycardia, heart block greater than first degree, cardiogenic shock, and overt cardiac failure. (See WARNINGS.)

TENORMIN is contraindicated in those patients with a history of hypersensitivity to the atenolol or any of the drug product’s components.

WARNINGS

Cardiac Failure

Sympathetic stimulation is necessary in supporting circulatory function in congestive heart failure, and beta blockade carries the potential hazard of further depressing myocardial contractility and precipitating more severe failure.

In patients with acute myocardial infarction, cardiac failure which is not promptly and effectively controlled by 80 mg of intravenous furosemide or equivalent therapy is a contraindication to beta-blocker treatment.

In Patients Without a History of Cardiac Failure

Continued depression of the myocardium with beta-blocking agents over a period of time can, in some cases, lead to cardiac failure. At the first sign or symptom of impending cardiac failure, patients should be treated appropriately according to currently recommended guidelines, and the response observed closely. If cardiac failure continues despite adequate treatment, TENORMIN should be withdrawn. (See DOSAGE AND ADMINISTRATION.)

Cessation of Therapy with TENORMIN
Patients with coronary artery disease, who are being treated with TENORMIN, should be advised against abrupt discontinuation of therapy. Severe exacerbation of angina and the occurrence of myocardial infarction and ventricular arrhythmias have been reported in angina patients following the abrupt discontinuation of therapy with beta-blockers. The last two complications may occur with or without preceding exacerbation of the angina pectoris. As with other beta-blockers, when discontinuation of TENORMIN is planned, the patients should be carefully observed and advised to limit physical activity to a minimum. If the angina worsens or acute coronary insufficiency develops, it is recommended that TENORMIN be promptly reinstituted, at least temporarily. Because coronary artery disease is common and may be unrecognized, it may be prudent not to discontinue TENORMIN therapy abruptly even in patients treated only for hypertension. (See DOSAGE AND ADMINISTRATION.)

Concomitant Use of Calcium Channel Blockers

Bradycardia and heart block can occur and the left ventricular end diastolic pressure can rise when beta-blockers are administered with verapamil or diltiazem. Patients with pre-existing conduction abnormalities or left ventricular dysfunction are particularly susceptible. (See PRECAUTIONS.)

Bronchospastic Diseases

PATIENTS WITH BRONCHOSPASTIC DISEASE SHOULD, IN GENERAL, NOT RECEIVE BETA-BLOCKERS. Because of its relative beta1 selectivity, however, TENORMIN may be used with caution in patients with bronchospastic disease who do not respond to, or cannot tolerate, other antihypertensive treatment. Since beta1 selectivity is not absolute, the lowest possible dose of TENORMIN should be used with therapy initiated at 50 mg and a beta2-stimulating agent (bronchodilator) should be made available. If dosage must be increased, dividing the dose should be considered in order to achieve lower peak blood levels.

Major Surgery

Chronically administered beta-blocking therapy should not be routinely withdrawn prior to major surgery, however the impaired ability of the heart to respond to reflex adrenergic stimuli may augment the risks of general anesthesia and surgical procedures.

Hypoglycemia

Beta-blockers may prevent early warning signs of hypoglycemia, such as tachycardia, and increase the risk for severe or prolonged hypoglycemia at any time during treatment, especially in patients with diabetes mellitus or children and patients who are fasting (i.e., surgery, not eating regularly, or are vomiting). If severe hypoglycemia occurs, patients should be instructed to seek emergency treatment.

Thyrotoxicosis

Beta-adrenergic blockade may mask certain clinical signs (e.g., tachycardia) of hyperthyroidism. Abrupt withdrawal of beta blockade might precipitate a thyroid storm; therefore, patients suspected of developing thyrotoxicosis from whom TENORMIN therapy is to be withdrawn should be monitored closely. (See DOSAGE AND ADMINISTRATION.)

Untreated Pheochromocytoma

TENORMIN should not be given to patients with untreated pheochromocytoma.

Pregnancy and Fetal Injury

Atenolol can cause fetal harm when administered to a pregnant woman. Atenolol crosses the placental barrier and appears in cord blood. Administration of atenolol, starting in the second trimester of pregnancy, has been associated with the birth of infants that are small for gestational age. No studies have been performed on the use of atenolol in the first trimester and the possibility of fetal injury cannot be excluded. If this drug is used during pregnancy, or if the patient becomes pregnant while taking this drug, the patient should be apprised of the potential hazard to the fetus.

Neonates born to mothers who are receiving TENORMIN at parturition or breastfeeding may be at risk for hypoglycemia and bradycardia. Caution should be exercised when TENORMIN is administered during pregnancy or to a woman who is breastfeeding. (See PRECAUTIONS, Nursing Mothers.)

Atenolol has been shown to produce a dose-related increase in embryo/fetal resorptions in rats at doses equal to or greater than 50 mg/kg/day or 25 or more times the maximum recommended human antihypertensive dose.* Although similar effects were not seen in rabbits, the compound was not evaluated in rabbits at doses above 25 mg/kg/day or 12.5 times the maximum recommended human antihypertensive dose.*

PRECAUTIONS

General

Patients already on a beta-blocker must be evaluated carefully before TENORMIN is administered. Initial and subsequent TENORMIN dosages can be adjusted downward depending on clinical observations including pulse and blood pressure. TENORMIN may aggravate peripheral arterial circulatory disorders.

Impaired Renal Function

The drug should be used with caution in patients with impaired renal function. (See DOSAGE AND ADMINISTRATION.)

*Based on the maximum dose of 100 mg/day in a 50 kg patient.

Information for Patients

Hypoglycemia

Inform patients or caregivers that there is a risk of hypoglycemia when TENORMIN is given to patients who are fasting or who are vomiting. Monitor for symptoms of hypoglycemia.

Drug Interactions

Catecholamine-depleting drugs (e.g., reserpine) may have an additive effect when given with beta-blocking agents. Patients treated with TENORMIN plus a catecholamine depletor should therefore be closely observed for evidence of hypotension and/or marked bradycardia which may produce vertigo, syncope, or postural hypotension.

Calcium channel blockers may also have an additive effect when given with TENORMIN (see WARNINGS).

Disopyramide is a Type I antiarrhythmic drug with potent negative inotropic and chronotropic effects. Disopyramide has been associated with severe bradycardia, asystole and heart failure when administered with beta-blockers.

Amiodarone is an antiarrhythmic agent with negative chronotropic properties that may be additive to those seen with beta-blockers.

Beta-blockers may exacerbate the rebound hypertension which can follow the withdrawal of clonidine. If the two drugs are coadministered, the beta-blocker should be withdrawn several days before the gradual withdrawal of clonidine. If replacing clonidine by beta-blocker therapy, the introduction of beta-blockers should be delayed for several days after clonidine administration has stopped.

Concomitant use of prostaglandin synthase inhibiting drugs, e.g., indomethacin, may decrease the hypotensive effects of beta-blockers.

Information on concurrent usage of atenolol and aspirin is limited. Data from several studies, i.e., TIMI-II, ISIS-2, currently do not suggest any clinical interaction between aspirin and beta-blockers in the acute myocardial infarction setting.

While taking beta-blockers, patients with a history of anaphylactic reaction to a variety of allergens may have a more severe reaction on repeated challenge, either accidental, diagnostic or therapeutic. Such patients may be unresponsive to the usual doses of epinephrine used to treat the allergic reaction.

Both digitalis glycosides and beta-blockers slow atrioventricular conduction and decrease heart rate. Concomitant use can increase the risk of bradycardia.

Carcinogenesis, Mutagenesis, Impairment of Fertility

Two long-term (maximum dosing duration of 18 or 24 months) rat studies and one long-term (maximum dosing duration of 18 months) mouse study, each employing dose levels as high as 300 mg/kg/day or 150 times the maximum recommended human antihypertensive dose,* did not indicate a carcinogenic potential of atenolol. A third (24 month) rat study, employing doses of 500 mg/kg/day and 1,500 mg/kg/day (250 and 750 times the maximum recommended human antihypertensive dose*) resulted in increased incidences of benign adrenal medullary tumors in males and females, mammary fibroadenomas in females, and anterior pituitary adenomas and thyroid parafollicular cell carcinomas in males. No evidence of a mutagenic potential of atenolol was uncovered in the dominant lethal test (mouse), in vivo cytogenetics test (Chinese hamster) or Ames test (S typhimurium).

Fertility of male or female rats (evaluated at dose levels as high as 200 mg/kg/day or 100 times the maximum recommended human dose*) was unaffected by atenolol administration.

Animal Toxicology

Chronic studies employing oral atenolol performed in animals have revealed the occurrence of vacuolation of epithelial cells of Brunner’s glands in the duodenum of both male and female dogs at all tested dose levels of atenolol (starting at 15 mg/kg/day or 7.5 times the maximum recommended human antihypertensive dose*) and increased incidence of atrial degeneration of hearts of male rats at 300 but not 150 mg atenolol/kg/day (150 and 75 times the maximum recommended human antihypertensive dose,* respectively).

Pregnancy

See WARNINGS - Pregnancy and Fetal Injury.

*Based on the maximum dose of 100 mg/day in a 50 kg patient.

Nursing Mothers

Atenolol is excreted in human breast milk at a ratio of 1.5 to 6.8 when compared to the concentration in plasma. Caution should be exercised when TENORMIN is administered to a nursing woman. Clinically significant bradycardia has been reported in breastfed infants. Premature infants, or infants with impaired renal function, may be more likely to develop adverse effects.

Neonates born to mothers who are receiving TENORMIN at parturition or breastfeeding may be at risk for hypoglycemia and bradycardia. Caution should be exercised when TENORMIN is administered during pregnancy or to a woman who is breastfeeding (See WARNINGS, Pregnancy and Fetal Injury).

Pediatric Use

Safety and effectiveness in pediatric patients have not been established.

Geriatric Use

Hypertension and Angina Pectoris Due to Coronary Atherosclerosis:

Clinical studies of TENORMIN did not include sufficient number of patients aged 65 and over to determine whether they respond differently from younger subjects. Other reported clinical experience has not identified differences in responses between the elderly and younger patients. In general, dose selection for an elderly patient should be cautious, usually starting at the low end of the dosing range, reflecting the greater frequency of decreased hepatic, renal, or cardiac function, and of concomitant disease or other drug therapy.

Acute Myocardial Infarction:

Of the 8,037 patients with suspected acute myocardial infarction randomized to TENORMIN in the ISIS-1 trial (See CLINICAL PHARMACOLOGY), 33% (2,644) were 65 years of age and older. It was not possible to identify significant differences in efficacy and safety between older and younger patients; however, elderly patients with systolic blood pressure < 120 mmHg seemed less likely to benefit (See INDICATIONS AND USAGE).

In general, dose selection for an elderly patient should be cautious, usually starting at the low end of the dosing range, reflecting greater frequency of decreased hepatic, renal, or cardiac function, and of concomitant disease or other drug therapy. Evaluation of patients with hypertension or myocardial infarction should always include assessment of renal function.

ADVERSE REACTIONS

Most adverse effects have been mild and transient.

The frequency estimates in the following table were derived from controlled studies in hypertensive patients in which adverse reactions were either volunteered by the patient (US studies) or elicited, e.g., by checklist (foreign studies). The reported frequency of elicited adverse effects was higher for both TENORMIN and placebo-treated patients than when these reactions were volunteered. Where frequency of adverse effects of TENORMIN and placebo is similar, causal relationship to TENORMIN is uncertain.

 | Volunteered; (US Studies) |  | Total − Volunteered; and Elicited; (Foreign + US Studies)
 | Atenolol; (n=164); % | Placebo; (n=206); % | Atenolol; (n=399); % | Placebo; (n=407); %
CARDIOVASCULAR
Bradycardia | 3 | 0 | 3 | 0
Cold Extremities | 0 | 0.5 | 12 | 5
Postural Hypotension | 2 | 1 | 4 | 5
Leg Pain | 0 | 0.5 | 3 | 1
CENTRAL NERVOUS SYSTEM/; NEUROMUSCULAR
Dizziness | 4 | 1 | 13 | 6
Vertigo | 2 | 0.5 | 2 | 0.2
Light-headedness | 1 | 0 | 3 | 0.7
Tiredness | 0.6 | 0.5 | 26 | 13
Fatigue | 3 | 1 | 6 | 5
Lethargy | 1 | 0 | 3 | 0.7
Drowsiness | 0.6 | 0 | 2 | 0.5
Depression | 0.6 | 0.5 | 12 | 9
Dreaming | 0 | 0 | 3 | 1
GASTROINTESTINAL
Diarrhea | 2 | 0 | 3 | 2
Nausea | 4 | 1 | 3 | 1
RESPIRATORY (See WARNINGS)
Wheeziness | 0 | 0 | 3 | 3
Dyspnea | 0.6 | 1 | 6 | 4

Acute Myocardial Infarction

In a series of investigations in the treatment of acute myocardial infarction, bradycardia and hypotension occurred more commonly, as expected for any beta-blocker, in atenolol-treated patients than in control patients. However, these usually responded to atropine and/or to withholding further dosage of atenolol. The incidence of heart failure was not increased by atenolol. Inotropic agents were infrequently used. The reported frequency of these and other events occurring during these investigations is given in the following table.

In a study of 477 patients, the following adverse events were reported during either intravenous and/or oral atenolol administration:

 | Conventional Therapy; Plus Atenolol (n=244) |  | Conventional; Therapy Alone (n=233)
Bradycardia | 43 | (18%) | 24 | (10%)
Hypotension | 60 | (25%) | 34 | (15%)
Bronchospasm | 3 | (1.2%) | 2 | (0.9%)
Heart Failure | 46 | (19%) | 56 | (24%)
Heart Block | 11 | (4.5%) | 10 | (4.3%)
BBB + Major; Axis Deviation | 16 | (6.6%) | 28 | (12%)
Supraventricular; Tachycardia | 28 | (11.5%) | 45 | (19%)
Atrial Fibrillation | 12 | (5%) | 29 | (11%)
Atrial Flutter | 4 | (1.6%) | 7 | (3%)
Ventricular; Tachycardia | 39 | (16%) | 52 | (22%)
Cardiac Reinfarction | 0 | (0%) | 6 | (2.6%)
Total Cardiac Arrests | 4 | (1.6%) | 16 | (6.9%)
Nonfatal Cardiac; Arrests | 4 | (1.6%) | 12 | (5.1%)
Deaths | 7 | (2.9%) | 16 | (6.9%)
Cardiogenic Shock | 1 | (0.4%) | 4 | (1.7%)
Development of Ventricular Septal; Defect | 0 | (0%) | 2 | (0.9%)
Development of; Mitral Regurgitation | 0 | (0%) | 2 | (0.9%)
Renal Failure | 1 | (0.4%) | 0 | (0%)
Pulmonary Emboli | 3 | (1.2%) | 0 | (0%)

In the subsequent International Study of Infarct Survival (ISIS-1) including over 16,000 patients of whom 8,037 were randomized to receive TENORMIN treatment, the dosage of intravenous and subsequent oral TENORMIN was either discontinued or reduced for the following reasons:

 | Reasons for Reduced Dosage
 | I.V. Atenolol; Reduced Dose; (<5 mg) [Full dosage was 10 mg and some patients received less than 10 mg but more than 5 mg.] |  | Oral Partial; Dose
Hypotension/Bradycardia | 105 | (1.3%) | 1168 | (14.5%)
Cardiogenic Shock | 4 | (.04%) | 35 | (.44%)
Reinfarction | 0 | (0%) | 5 | (.06%)
Cardiac Arrest | 5 | (.06%) | 28 | (.34%)
Heart Block (> first degree) | 5 | (.06%) | 143 | (1.7%)
Cardiac Failure | 1 | (.01%) | 233 | (2.9%)
Arrhythmias | 3 | (.04%) | 22 | (.27%)
Bronchospasm | 1 | (.01%) | 50 | (.62%)

During postmarketing experience with TENORMIN, the following have been reported in temporal relationship to the use of the drug: elevated liver enzymes and/or bilirubin, hallucinations, headache, impotence, Peyronie's disease, postural hypotension which may be associated with syncope, psoriasiform rash or exacerbation of psoriasis, psychoses, purpura, reversible alopecia, thrombocytopenia, visual disturbance, sick sinus syndrome, and dry mouth. TENORMIN, like other beta-blockers, has been associated with the development of antinuclear antibodies (ANA), lupus syndrome, and Raynaud’s phenomenon.

POTENTIAL ADVERSE EFFECTS

In addition, a variety of adverse effects have been reported with other beta-adrenergic blocking agents, and may be considered potential adverse effects of TENORMIN.

Hematologic: Agranulocytosis.

Allergic: Fever, combined with aching and sore throat, laryngospasm, and respiratory distress.

Central Nervous System: Reversible mental depression progressing to catatonia; an acute reversible syndrome characterized by disorientation of time and place; short-term memory loss; emotional lability with slightly clouded sensorium; and, decreased performance on neuropsychometrics.

Gastrointestinal: Mesenteric arterial thrombosis, ischemic colitis.

Other: Erythematous rash.

Miscellaneous: There have been reports of skin rashes and/or dry eyes associated with the use of beta-adrenergic blocking drugs. The reported incidence is small, and in most cases, the symptoms have cleared when treatment was withdrawn. Discontinuance of the drug should be considered if any such reaction is not otherwise explicable. Patients should be closely monitored following cessation of therapy. (See DOSAGE AND ADMINISTRATION).

The oculomucocutaneous syndrome associated with the beta-blocker practolol has not been reported with TENORMIN. Furthermore, a number of patients who had previously demonstrated established practolol reactions were transferred to TENORMIN therapy with subsequent resolution or quiescence of the reaction.

To report SUSPECTED ADVERSE REACTIONS, contact TWi Pharmaceuticals, Inc. at 1-844-518-2989 or FDA at 1-800-FDA-1088 or www.fda.gov/medwatch for voluntary reporting of adverse reactions.

OVERDOSAGE

Overdosage with TENORMIN has been reported with patients surviving acute doses as high as 5 g. One death was reported in a man who may have taken as much as 10 g acutely.

The predominant symptoms reported following TENORMIN overdose are lethargy, disorder of respiratory drive, wheezing, sinus pause and bradycardia. Additionally, common effects associated with overdosage of any beta-adrenergic blocking agent and which might also be expected in TENORMIN overdose are congestive heart failure, hypotension, bronchospasm and/or hypoglycemia.

Treatment of overdose should be directed to the removal of any unabsorbed drug by induced emesis, gastric lavage, or administration of activated charcoal. TENORMIN can be removed from the general circulation by hemodialysis. Other treatment modalities should be employed at the physician's discretion and may include:

BRADYCARDIA: Atropine intravenously. If there is no response to vagal blockade, give isoproterenol cautiously. In refractory cases, a transvenous cardiac pacemaker may be indicated.

HEART BLOCK (SECOND OR THIRD DEGREE): Isoproterenol or transvenous cardiac pacemaker.

CARDIAC FAILURE: Digitalize the patient and administer a diuretic. Glucagon has been reported to be useful.

HYPOTENSION: Vasopressors such as dopamine or norepinephrine (levarterenol). Monitor blood pressure continuously.

BRONCHOSPASM: A beta2 stimulant such as isoproterenol or terbutaline and/or aminophylline.

HYPOGLYCEMIA: Intravenous glucose.

Based on the severity of symptoms, management may require intensive support care and facilities for applying cardiac and respiratory support.

DOSAGE AND ADMINISTRATION

Hypertension

The initial dose of TENORMIN is 50 mg given as one tablet a day either alone or added to diuretic therapy. The full effect of this dose will usually be seen within one to two weeks. If an optimal response is not achieved, the dosage should be increased to TENORMIN 100 mg given as one tablet a day. Increasing the dosage beyond 100 mg a day is unlikely to produce any further benefit.

TENORMIN may be used alone or concomitantly with other antihypertensive agents including thiazide-type diuretics, hydralazine, prazosin, and alpha-methyldopa.

Angina Pectoris

The initial dose of TENORMIN is 50 mg given as one tablet a day. If an optimal response is not achieved within one week, the dosage should be increased to TENORMIN 100 mg given as one tablet a day. Some patients may require a dosage of 200 mg once a day for optimal effect.

Twenty-four hour control with once daily dosing is achieved by giving doses larger than necessary to achieve an immediate maximum effect. The maximum early effect on exercise tolerance occurs with doses of 50 mg to 100 mg, but at these doses the effect at 24 hours is attenuated, averaging about 50% to 75% of that observed with once a day oral doses of 200 mg.

Acute Myocardial Infarction

In patients with definite or suspected acute myocardial infarction, treatment with TENORMIN I.V. Injection should be initiated as soon as possible after the patient's arrival in the hospital and after eligibility is established. Such treatment should be initiated in a coronary care or similar unit immediately after the patient's hemodynamic condition has stabilized. Treatment should begin with the intravenous administration of 5 mg TENORMIN over 5 minutes followed by another 5 mg intravenous injection 10 minutes later. TENORMIN I.V. Injection should be administered under carefully controlled conditions including monitoring of blood pressure, heart rate, and electrocardiogram. Dilutions of TENORMIN I.V. Injection in Dextrose Injection USP, Sodium Chloride Injection USP, or Sodium Chloride and Dextrose Injection may be used. These admixtures are stable for 48 hours if they are not used immediately.

In patients who tolerate the full intravenous dose (10 mg), TENORMIN Tablets 50 mg should be initiated 10 minutes after the last intravenous dose followed by another 50 mg oral dose 12 hours later. Thereafter, TENORMIN can be given orally either 100 mg once daily or 50 mg twice a day for a further 6 to 9 days or until discharge from the hospital. If bradycardia or hypotension requiring treatment or any other untoward effects occur, TENORMIN should be discontinued. (See full prescribing information prior to initiating therapy with TENORMIN Tablets.)

Data from other beta-blocker trials suggest that if there is any question concerning the use of I.V. beta-blocker or clinical estimate that there is a contraindication, the I.V. beta-blocker may be eliminated and patients fulfilling the safety criteria may be given TENORMIN Tablets 50 mg twice daily or 100 mg once a day for at least seven days (if the I.V. dosing is excluded).

Although the demonstration of efficacy of TENORMIN is based entirely on data from the first seven postinfarction days, data from other beta-blocker trials suggest that treatment with beta-blockers that are effective in the postinfarction setting may be continued for one to three years if there are no contraindications.

TENORMIN is an additional treatment to standard coronary care unit therapy.

Elderly Patients or Patients with Renal Impairment

TENORMIN is excreted by the kidneys; consequently dosage should be adjusted in cases of severe impairment of renal function. In general, dose selection for an elderly patient should be cautious, usually starting at the low end of the dosing range, reflecting greater frequency of decreased hepatic, renal, or cardiac function, and of concomitant disease or other drug therapy. Evaluation of patients with hypertension or myocardial infarction should always include assessment of renal function. Atenolol excretion would be expected to decrease with advancing age.

No significant accumulation of TENORMIN occurs until creatinine clearance falls below 35 mL/min/1.73m^2. Accumulation of atenolol and prolongation of its half-life were studied in subjects with creatinine clearance between 5 mL/min and 105 mL/min. Peak plasma levels were significantly increased in subjects with creatinine clearances below 30 mL/min.

The following maximum oral dosages are recommended for elderly, renally-impaired patients and for patients with renal impairment due to other causes:

Creatinine Clearance; (mL/min/1.73m^2) | Atenolol; Elimination Half-Life; (h) | Maximum Dosage
15-35 | 16-27 | 50 mg daily
<15 | >27 | 25 mg daily

Some renally-impaired or elderly patients being treated for hypertension may require a lower starting dose of TENORMIN: 25 mg given as one tablet a day. If this 25 mg dose is used, assessment of efficacy must be made carefully. This should include measurement of blood pressure just prior to the next dose ("trough" blood pressure) to ensure that the treatment effect is present for a full 24 hours.

Although a similar dosage reduction may be considered for elderly and/or renally-impaired patients being treated for indications other than hypertension, data are not available for these patient populations.

Patients on hemodialysis should be given 25 mg or 50 mg after each dialysis; this should be done under hospital supervision as marked falls in blood pressure can occur.

Cessation of Therapy in Patients with Angina Pectoris

If withdrawal of TENORMIN therapy is planned, it should be achieved gradually and patients should be carefully observed and advised to limit physical activity to a minimum.

HOW SUPPLIED

TENORMIN Tablets

Tablets of 25 mg atenolol are round, flat, uncoated white tablets identified with "T" debossed on one side and 107 debossed on the other side, supplied in bottles of 90 tablets (NDC 24979-244-07).

Tablets of 50 mg atenolol are round, flat, uncoated white tablets identified with "TENORMIN" debossed on one side and 105 debossed on the other side, bisected, supplied in bottles of 90 tablets (NDC 24979-245-07).

Tablets of 100 mg atenolol are round, flat, uncoated white tablets identified with "TENORMIN" debossed on one side and 101 debossed on the other side, supplied in bottles of 90 tablets (NDC 24979-246-07).

Store at controlled room temperature, 20°C to 25°C (68°F to 77°F) [see USP]. Dispense in well-closed, light-resistant containers.

TENORMIN is a trademark of TWi Pharmaceuticals, Inc.

Manufactured by:
Norwich Pharmaceuticals, Inc.
Norwich, NY 13815 USA

Distributed by:
TWi Pharmaceuticals USA, Inc.
Paramus, NJ 07652

Revised: 08/2024

PKG03120

PACKAGE/LABEL PRINCIPAL DISPLAY PANEL – 25 mg

NDC 24979-244-07

Rx Only

TENORMIN®
(atenolol)

25 mg tablets

90 Tablets

PACKAGE/LABEL PRINCIPAL DISPLAY PANEL – 50 mg

NDC 24979-245-07

Rx Only

TENORMIN®
(atenolol)

50 mg tablets

90 Tablets

PACKAGE/LABEL PRINCIPAL DISPLAY - 100 mg

NDC 24979-246-07

Rx Only

TENORMIN®
(atenolol)

100 mg tablets

90 Tablets